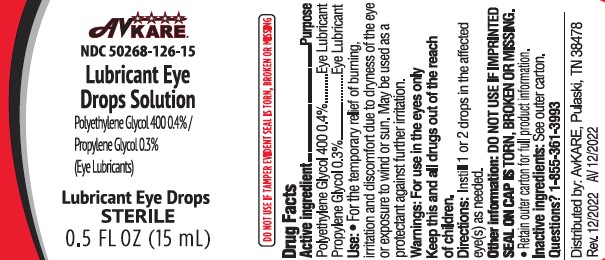 DRUG LABEL: Lubricant Eye Drops Solution
NDC: 50268-126 | Form: SOLUTION
Manufacturer: AvPAK
Category: otc | Type: HUMAN OTC DRUG LABEL
Date: 20260108

ACTIVE INGREDIENTS: POLYETHYLENE GLYCOL 400 4 mg/1 mL; PROPYLENE GLYCOL 3 mg/1 mL
INACTIVE INGREDIENTS: HYPROMELLOSE, UNSPECIFIED; BORIC ACID; CALCIUM CHLORIDE; MAGNESIUM CHLORIDE; POTASSIUM CHLORIDE; WATER; SODIUM CHLORIDE; ZINC CHLORIDE; BENZALKONIUM CHLORIDE

Lubricant Eye Drops Solution

ACTIVE INGREDIENT

Active Ingredients | Purpose
Polyethylene Glycol 400 0.4% | Lubricant
Propylene Glycol 0.3% | Lubricant

Uses

- For the temporary relief of burning, irritation and discomfort due to dryness of the eye and exposure to wind or sun.
- May be used as a protectant against further irritation.

Warnings

For use in the eyes only

Do not use

- If solution changes color or becomes cloudy.

When using this product

- avoid contamination, do not touch tip of container to any surface
- replace cap after use

Stop use and ask a doctor if

- you experience eye pain, changes in vision, continued redness or irritation of the eye
- the condition worsens or persists for more than 72 hours

KEEP OUT OF REACH OF CHILDREN

Keep this and all drugs out of the reach of children.
If swallowed, get medical help or contact a Poison Control Center right away (1-800-222-1222)

Directions

- shake well before use
- instill 1 or 2 drops in the affected eye(s) as needed

Other Information

- store at room temperature 15°- 30°C (59°-86°F).
- do not use if imprinted seal on cap is torn, broken or missing
- discard 90 days after opening
- retain outer carton for full product information

Inactive Ingredients:

Benzalkonium chloride (preservative), boric acid, calcium chloride, hypromellose, magnesium chloride, potassium chloride, purified water, sodium chloride, zinc chloride. May contain hydrochloric acid and/or sodium hydroxide to adjust pH.

Questions?

1-855-361-3993

Distributed by:

AvKARE

Pulaski, TN 38478

www.avkare.com

Rev. 12/2022 AV 12/2022